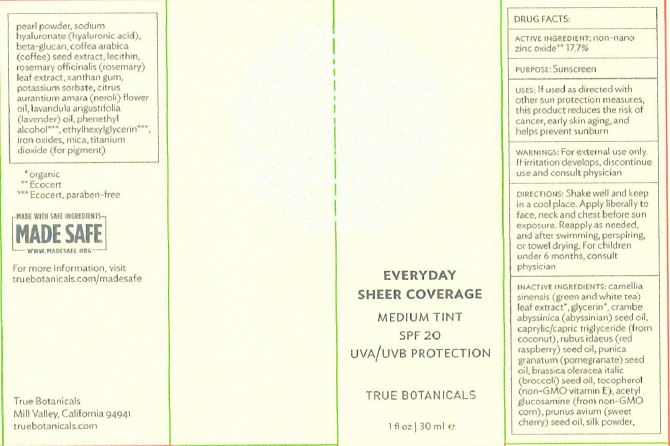 DRUG LABEL: Everyday Sheer Coverage Medium Tint SPF 20
NDC: 62742-4160 | Form: CREAM
Manufacturer: Allure Labs Inc
Category: otc | Type: HUMAN OTC DRUG LABEL
Date: 20171220

ACTIVE INGREDIENTS: ZINC OXIDE 177 mg/1 mL
INACTIVE INGREDIENTS: GREEN TEA LEAF; WHITE TEA; GLYCERIN; CRAMBE HISPANICA SUBSP. ABYSSINICA SEED OIL; MEDIUM-CHAIN TRIGLYCERIDES; RASPBERRY SEED OIL; POMEGRANATE SEED OIL; BROCCOLI SEED OIL; TOCOPHEROL; N-ACETYLGLUCOSAMINE; SWEET CHERRY SEED OIL; BOMBYX MORI FIBER; PEARL (HYRIOPSIS CUMINGII); HYALURONATE SODIUM; COFFEA ARABICA SEED, ROASTED; LECITHIN, SOYBEAN; ROSEMARY OIL; XANTHAN GUM; POTASSIUM SORBATE; LAVENDER OIL; PHENYLETHYL ALCOHOL; ETHYLHEXYLGLYCERIN; FERRIC OXIDE RED; FERRIC OXIDE YELLOW; FERROSOFERRIC OXIDE; TITANIUM DIOXIDE

Drug Facts

ACTIVE INGREDIENT

Non Nano Zinc Oxide - 17.7%

PURPOSE

Sunscreen

INDICATIONS AND USAGE

Uses: if used as directed with other sun protection measures, this product reduces the risk of cancer, early skin aging and helps prevent sunburn.

WARNINGS

for external use only. if irritation developes, discontinue use and consult physician.

DOSAGE AND ADMINISTRATION

Shake well and keep in a cool place. Apply liberally to face, neck and chest before sun exposure. Reapply as needed, and after swimming, perspirin or towel drying. For children under 6 months, consult physicain.

INACTIVE INGREDIENT

Camellia Sinensis (Green and White Tea) Leaf Extract, Glycerin, Crambe Abyssinica (Abyssinian Seed Oil, Caprylic/Capric Triglycerides (from Coconut), Rubus Idaeus (Red Raspberry) Seed Oil, Punica Granatum (Pomegranade) Seed Oil, Brassica Oleracea Italic (Broccoli) Seed Oil, Tocoperol (non-GMO Vitamin E), Acetyl Glucosamine (from non-GMO corn), Prunus Avium (Sweet Cherry Seed Oil), Silk Powder, Pearl Powder, Sodium Hyaluronate (Hyaluronic Acid), Beta-Glucan, Coffea Arabica (Coffee) Seed Extract, Lecithin, Rosemary Officinalis (Rosemary) Leaf Extract, Xanthan Gum, Potassium Sorbate, Citrus Aurantium Amara (Neroli) FLower Oil, Lavandula Angustifolia (Lavender) Oil, Phenethyl Alcohol, Ethylhexylglycerin, Iron Oxides, Mica, Titanium Dioxide (For Pigment).

PACKAGE LABEL

True Botanicals

Mill Valley, California 94941

truebotanicals.com